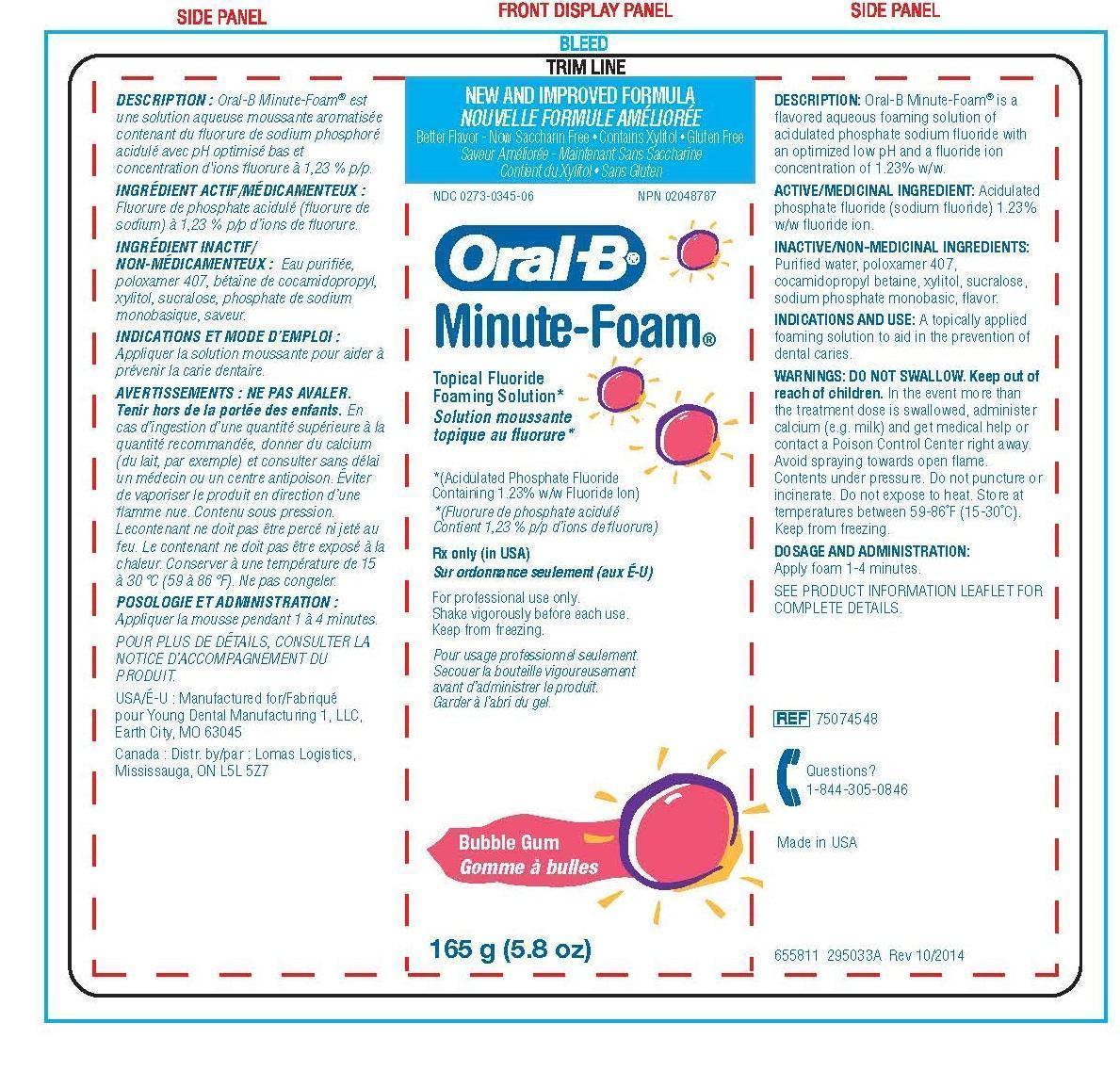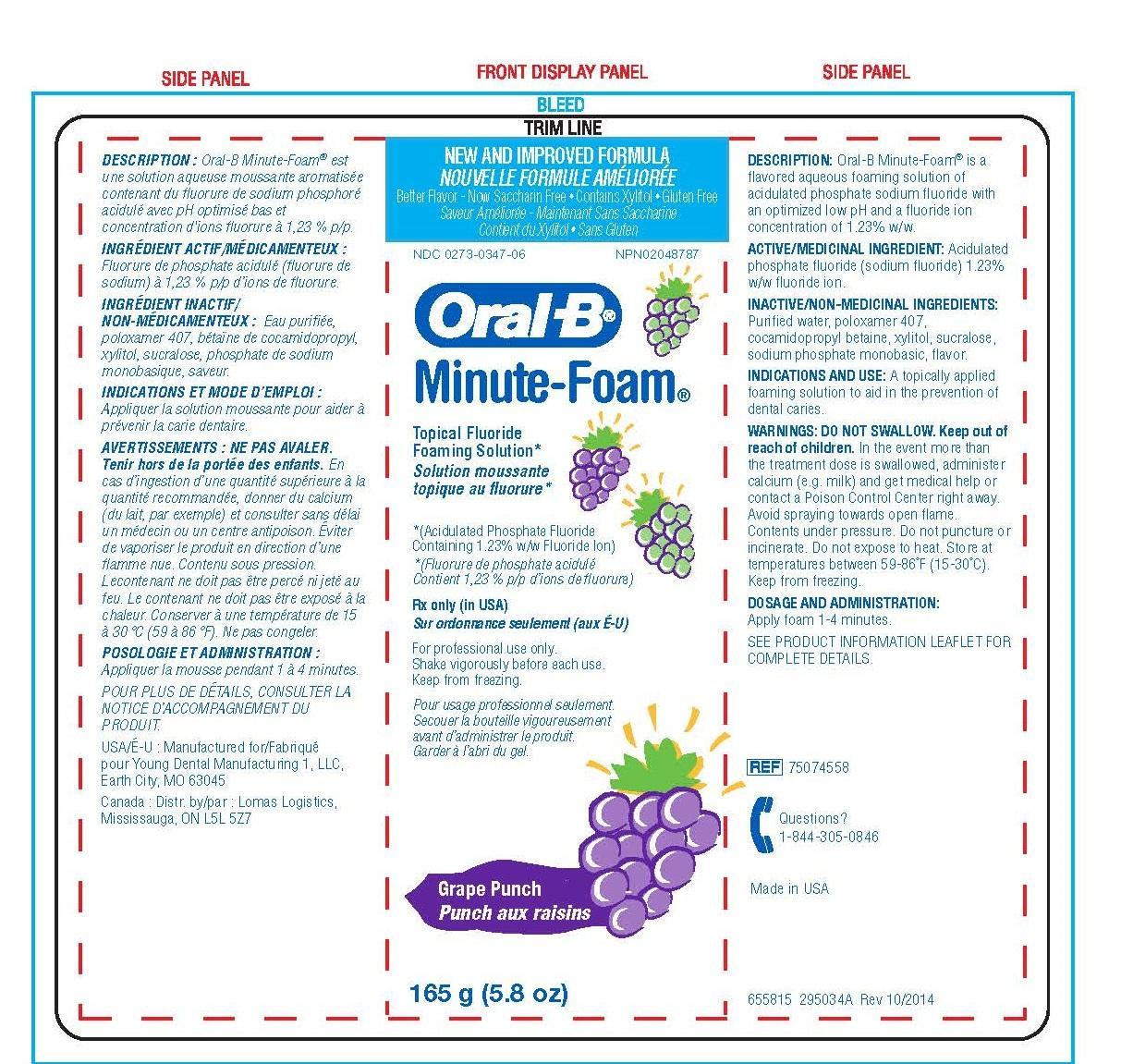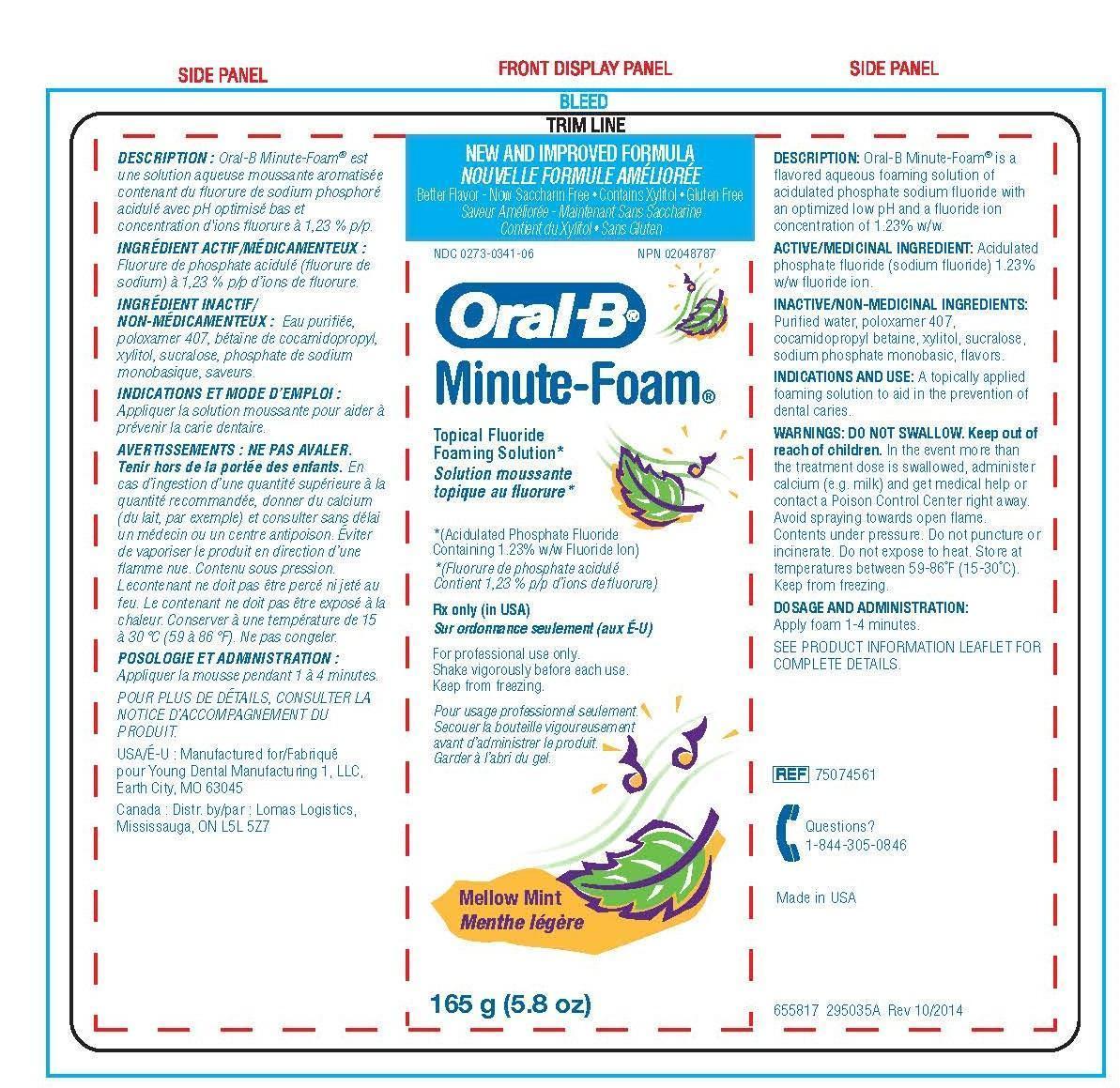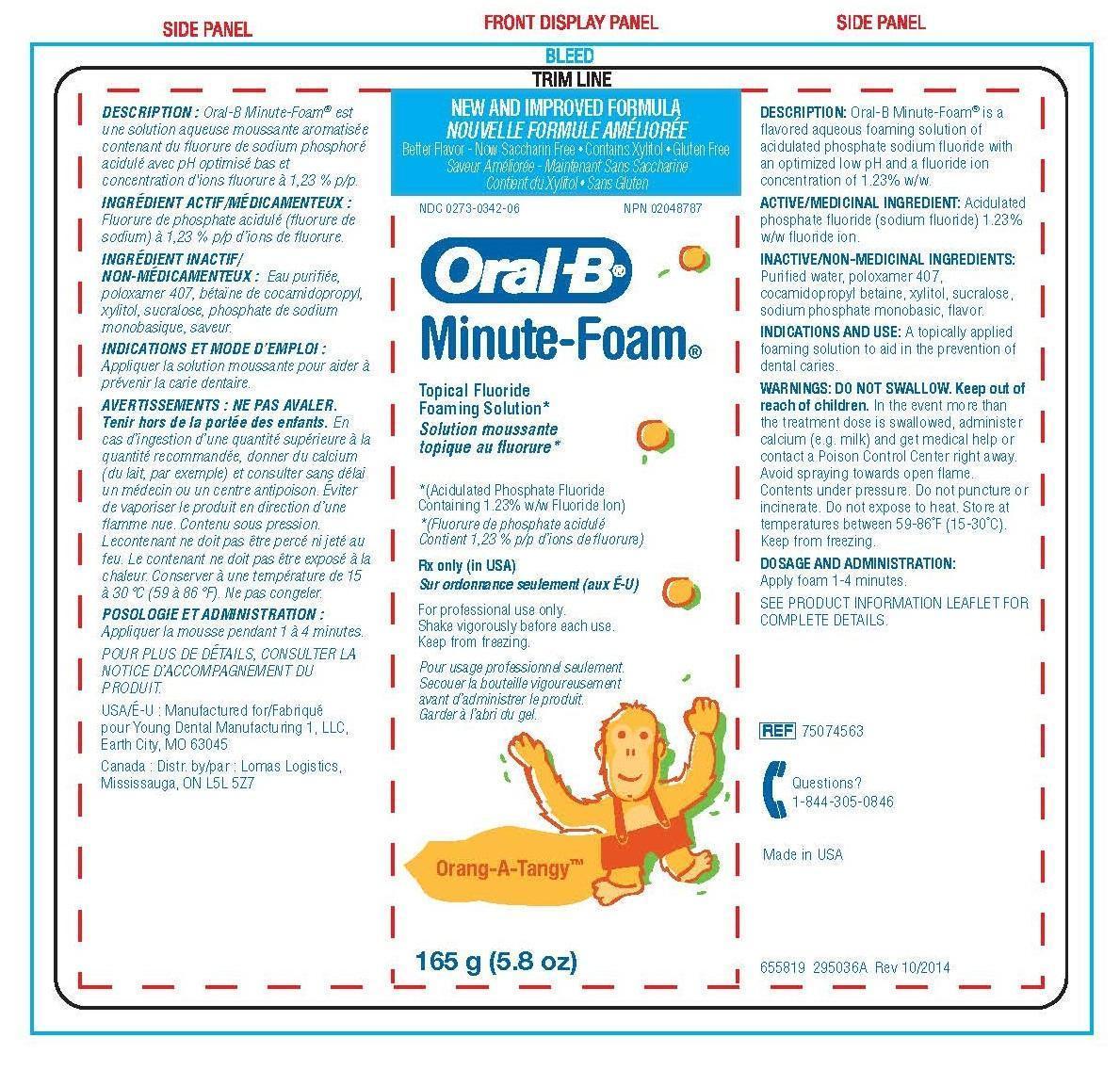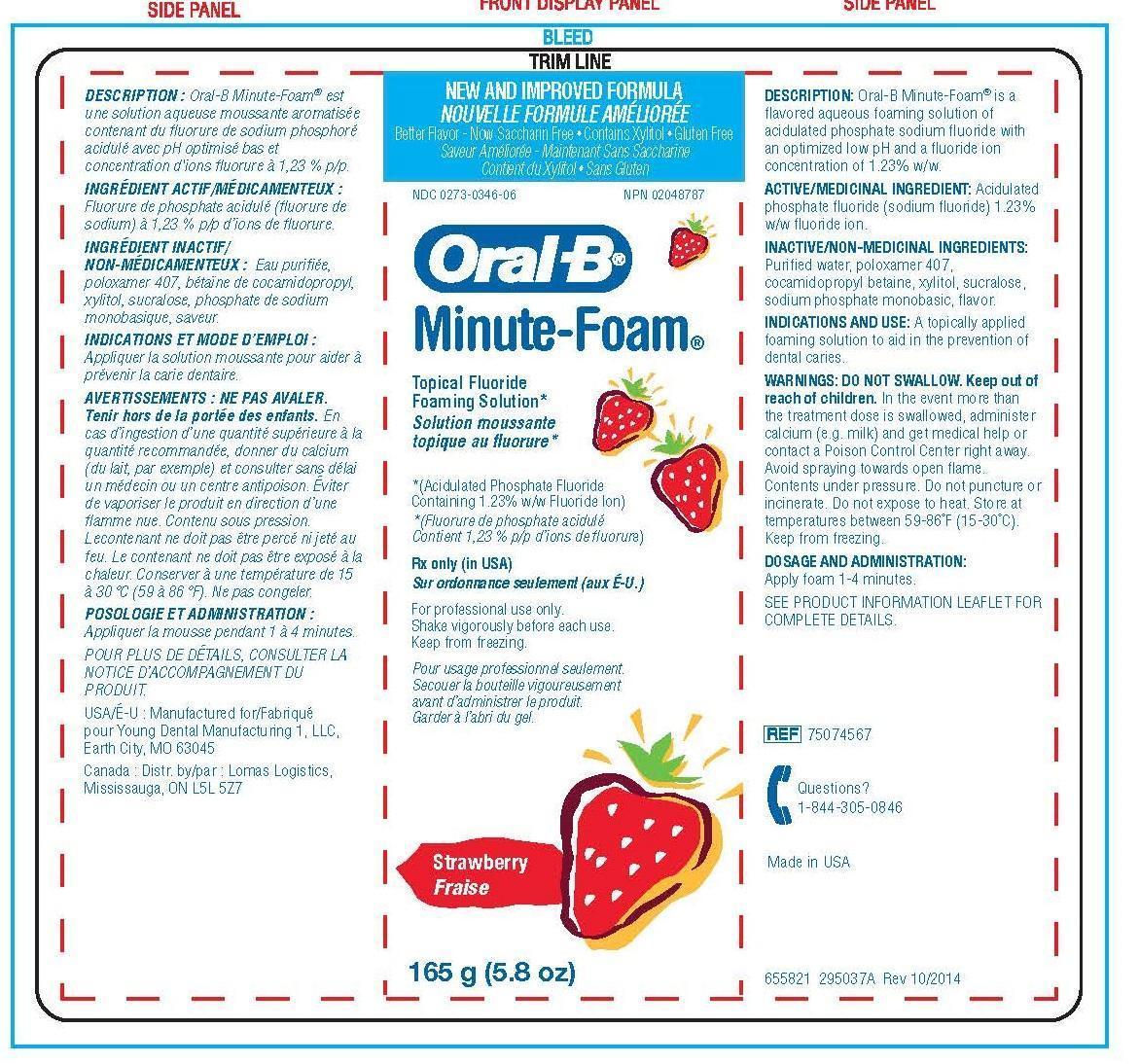 DRUG LABEL: Oral B Minute-Foam

NDC: 0273-0345 | Form: SOLUTION
Manufacturer: YOUNG DENTAL MANUFACTURING CO 1, LLC
Category: prescription | Type: HUMAN PRESCRIPTION DRUG LABEL
Date: 20230103

ACTIVE INGREDIENTS: SODIUM FLUORIDE 12.3 mg/1 g
INACTIVE INGREDIENTS: WATER; POLOXAMER 407; COCAMIDOPROPYL BETAINE; XYLITOL; SUCRALOSE; SODIUM PHOSPHATE, MONOBASIC

Oral B Minute-Foam Soultion

Description

Minute-Foam® is a flavored aqueous foaming solution of acidulated phosphate sodium fluoride with an optimized low pH and a fluoride ion

concentration of 1.23% w/w.

Inactives

- Purified water
- Poloxamer 407
- Cocamidoprophyl betaine
- Xylitol, sucralose
- Sodiumphosphate monobasic
- Flavor

Warnings

- DO NOT SWALLOW.
- Keep out of reach of children. In the event more than the treatment dose is swallowed, administer calcium (e.g.milk) and get medical help or contact a Poison Control Center right away. Avoid spraying towards open flame.
- Contents under pressure. Do not puncture or incinerate. Do not expose to heat.
- Store at temperatures between 59-86°F
- (15-30°C). Keep from freezing.